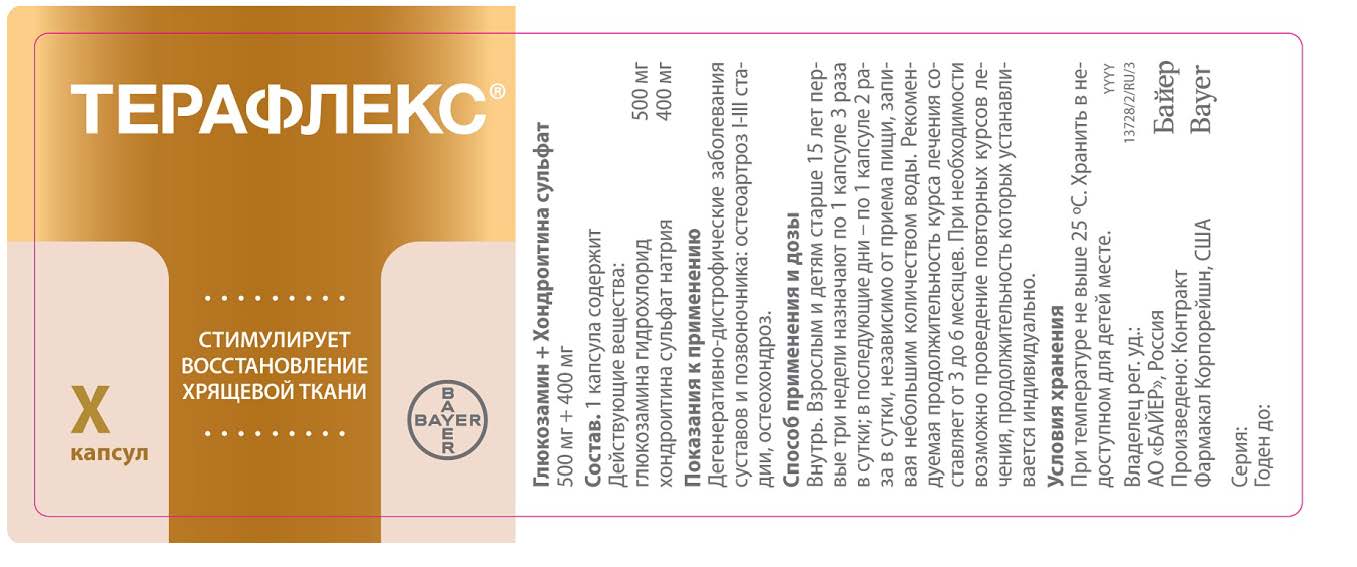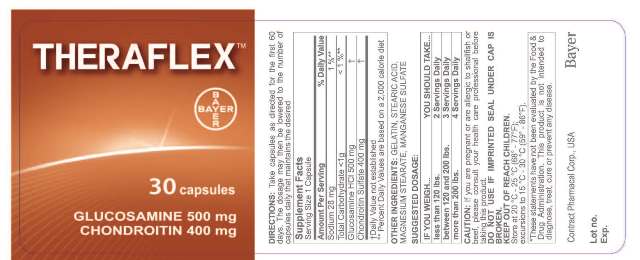 DRUG LABEL: THERAFLEX Glucosamine Plus Max
NDC: 61841-055 | Form: CAPSULE
Manufacturer: Bayer HealthCare LLC.
Category: otc | Type: HUMAN OTC DRUG LABEL
Date: 20260112

ACTIVE INGREDIENTS: CHONDROITIN SULFATE SODIUM (BOVINE) 500 mg/1 1
INACTIVE INGREDIENTS: MANGANESE SULFATE

THERAFLEX Glucosamine Plus Max Hard Gelatine Capsules